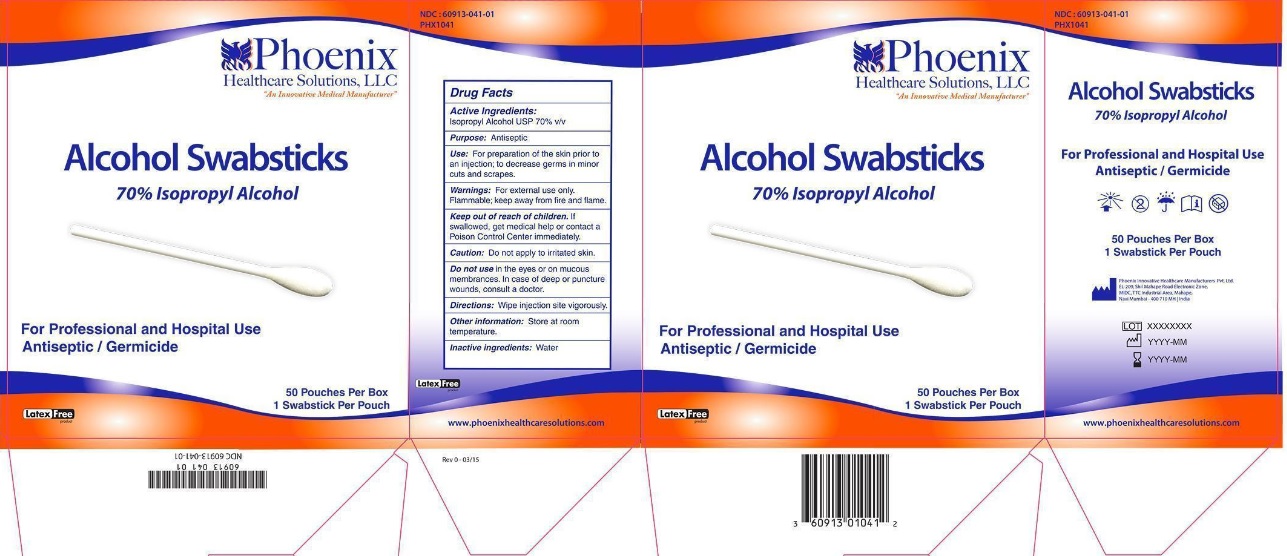 DRUG LABEL: Alcohol Swab Sticks
NDC: 60913-041 | Form: SWAB
Manufacturer: PHOENIX HEALTHCARE SOLUTIONS, LLC
Category: otc | Type: HUMAN OTC DRUG LABEL
Date: 20251023

ACTIVE INGREDIENTS: ISOPROPYL ALCOHOL 70 mL/100 mL
INACTIVE INGREDIENTS: WATER

Phoenix Alcohol Swabsticks

Active Ingredients

Isopropyl alcohol 70% v/v

Purpose

Antiseptic

Use:

For preparation of the skin prior to injection; to decrease germs in minor cuts and scrapes.

Warnings:

- For external use only. Flammable; keep away from fire and flame.

Keep out of reach of children.

If swallowed, get medical help or contact a Poison Control Center immediately.

Caution:

Do not apply to irritated skin.

Do not use

in the eyes, or on mucous membranes. In case of deep or puncture wounds, consult a doctor.

Directions:

Wipe injection site vigorously.

Other information:

Store at room temperature

Inactive ingredients:

Water

Principal Display Panel

NDC 60913-041-01

Phoenix Healthcare Solutions,LLC

"An Innovative Medical Manufacturer"

Alcohol Swabsticks

70% Isopropyl Alcohol

For Professional and Hospital Use

Antiseptic/Germicide

50 Pouches Per Box

1 Swabstick Per Pouch